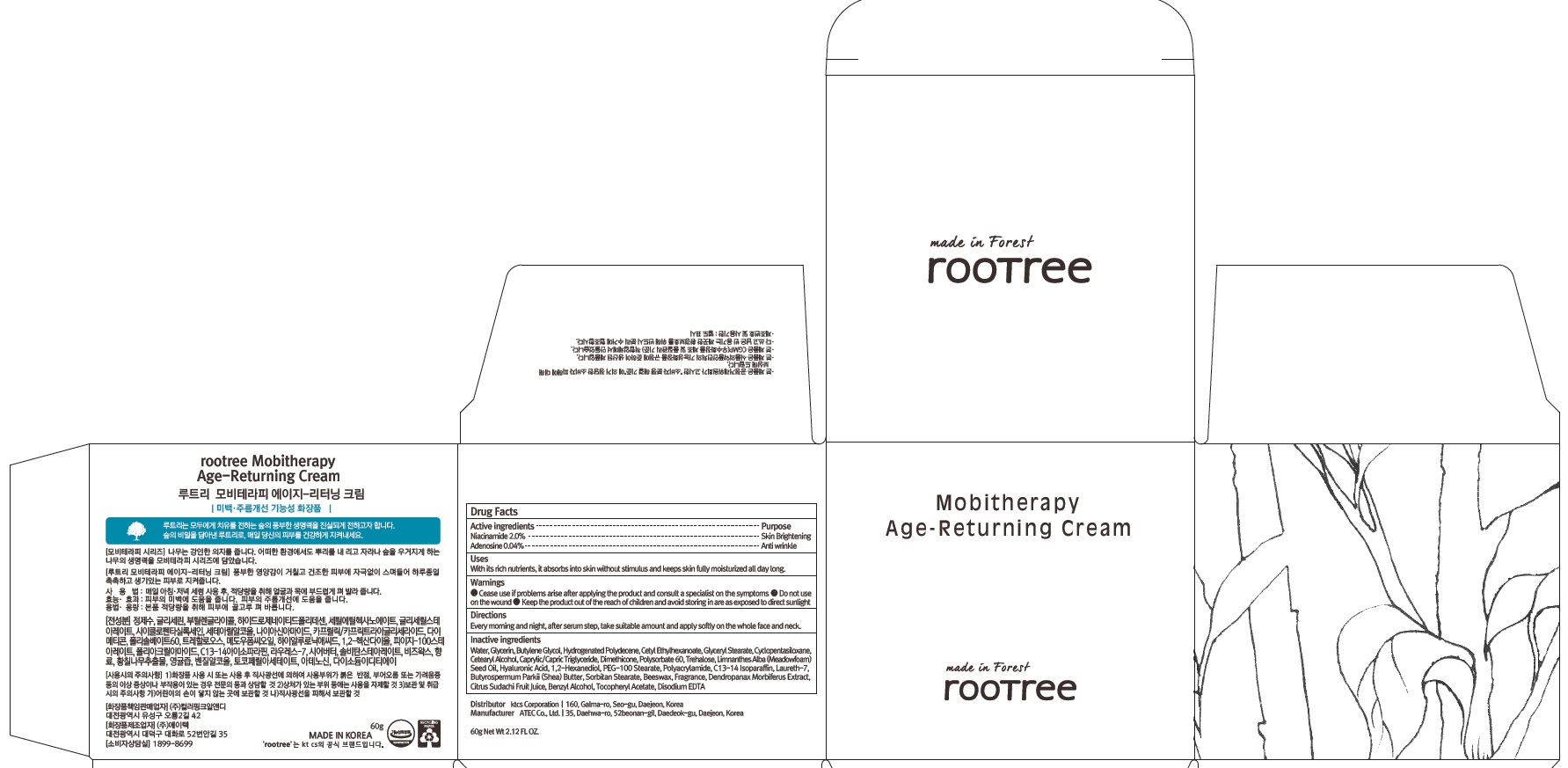 DRUG LABEL: rootree Mobitherapy Age Returning
NDC: 72441-050 | Form: CREAM
Manufacturer: KTCS Corporation
Category: otc | Type: HUMAN OTC DRUG LABEL
Date: 20201229

ACTIVE INGREDIENTS: Niacinamide 1.2 g/60 g; Adenosine 0.024 g/60 g
INACTIVE INGREDIENTS: Water; Glycerin

ACTIVE INGREDIENTS

Niacinamide 2.0%, Adenosine 0.04%

INACTIVE INGREDIENTS

Water, Glycerin, Butylene Glycol, Hydrogenated Polydecene, Cetyl Ethylhexanoate, Glyceryl Stearate, Cyclopentasiloxane, Cetearyl Alcohol, Caprylic/Capric Triglyceride, Dimethicone, Polysorbate 60, Trehalose, Limnanthes Alba (Meadowfoam) Seed Oil, Hyaluronic Acid, 1,2-Hexanediol, PEG-100 Stearate, Polyacrylamide, C13-14 Isoparaffin, Laureth-7, Butyrospermum Parkii (Shea) Butter, Sorbitan Stearate, Beeswax, Fragrance, Dendropanax Morbiferus Extract, Citrus Sudachi Fruit Juice, Benzyl Alcohol, Tocopheryl Acetate, Disodium EDTA

PURPOSE

Skin Brightening, Anti-wrinkle

WARNINGS

- Cease use if problems arise after applying the product and consult a specialist on the symptoms.

- Do not use on the wound.
- Keep the product out of the reach of children and avoid storing in are as exposed to direct sunlight.

KEEP OUT OF REACH OF CHILDREN

Keep the product out of the reach of children

Uses

With its rich nutrients, it absorbs into skin without stimulus and keeps skin fully moisturized all day long.

Directions

Every morning and night, after serum step, take suitable amount and apply softly on the whole face and neck.